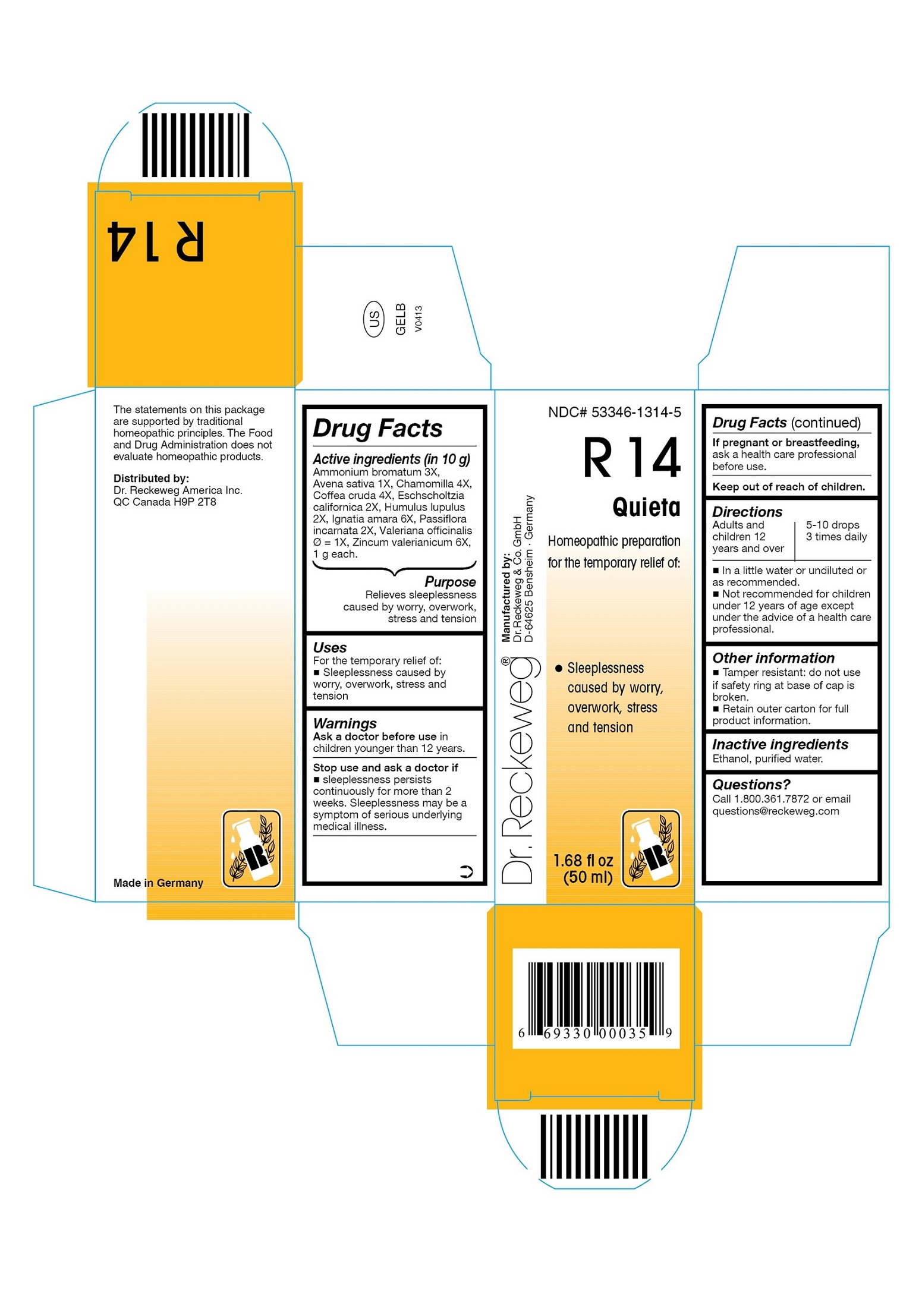 DRUG LABEL: DR. RECKEWEG R14 Quieta
NDC: 53346-1314 | Form: LIQUID
Manufacturer: PHARMAZEUTISCHE FABRIK DR. RECKEWEG & CO
Category: homeopathic | Type: HUMAN OTC DRUG LABEL
Date: 20130515

ACTIVE INGREDIENTS: AMMONIUM BROMIDE 3 [hp_X]/50 mL; AVENA SATIVA FLOWERING TOP 1 [hp_X]/50 mL; MATRICARIA RECUTITA 4 [hp_X]/50 mL; ARABICA COFFEE BEAN 4 [hp_X]/50 mL; ESCHSCHOLZIA CALIFORNICA FLOWERING TOP 2 [hp_X]/50 mL; HOPS 2 [hp_X]/50 mL; STRYCHNOS IGNATII SEED 6 [hp_X]/50 mL; PASSIFLORA INCARNATA FLOWERING TOP 2 [hp_X]/50 mL; VALERIAN 1 [hp_X]/50 mL; ZINC VALERATE DIHYDRATE 6 [hp_X]/50 mL
INACTIVE INGREDIENTS: ALCOHOL; WATER

DR. RECKEWEG R14 Quieta

Active ingredients

Ammonium bromatum 3X, Avena sativa 1X, Chamomilla 4X, Coffea cruda 4X, Eschscholtzia californica 2X, Humulus lupulus 2X, Ignatia amara 6X, Passiflora incarnata 2X,

Valeriana officinalis 1X, Zincum valerianicum 6X, 1 g each in 10 g.

Purpose

Relieves sleeplessness caused by worry, overwork, stress and tension

Uses

For the temporary relief of:

- Sleeplessness caused by worry, overwork, stress and tension

Warnings

Ask a doctor before use in children younger than 12 years.

Stop use and ask a doctor if

- sleeplessness persists continuously for more than 2 weeks
- sleeplessness may be a symptom of serious underlying medical illness.

PREGNANCY OR BREAST FEEDING

If pregnant or breastfeeding, ask a health care professional before use.

Keep out of reach of children.

Directions
Adults and children ≥ 12 years 5-10 drops 3 times daily in a little water or undiluted or as recommended.

Not recommended for children under 12 years of age except under the advice of a health care professional.

Other information

- Tamper resistant: do not use if safety ring at base of cap is broken.
- Retain outer carton for full product information.

Inactive ingredients

Ethanol, purified water.

Questions?

Call 1-800-361-7872 or email questions@reckeweg.com

PACKAGE LABEL

NDC# 53346-1314-5

Dr. Reckeweg R14 Quieta

Homeopathic preparation for the temporary relief of:

- Sleeplessness caused by worry, overwork, stress and tension

Manufactured by:

Dr. Reckeweg Co. GmbH

D-64625 Bensheim

Germany

1.68 fl oz
(50 ml)